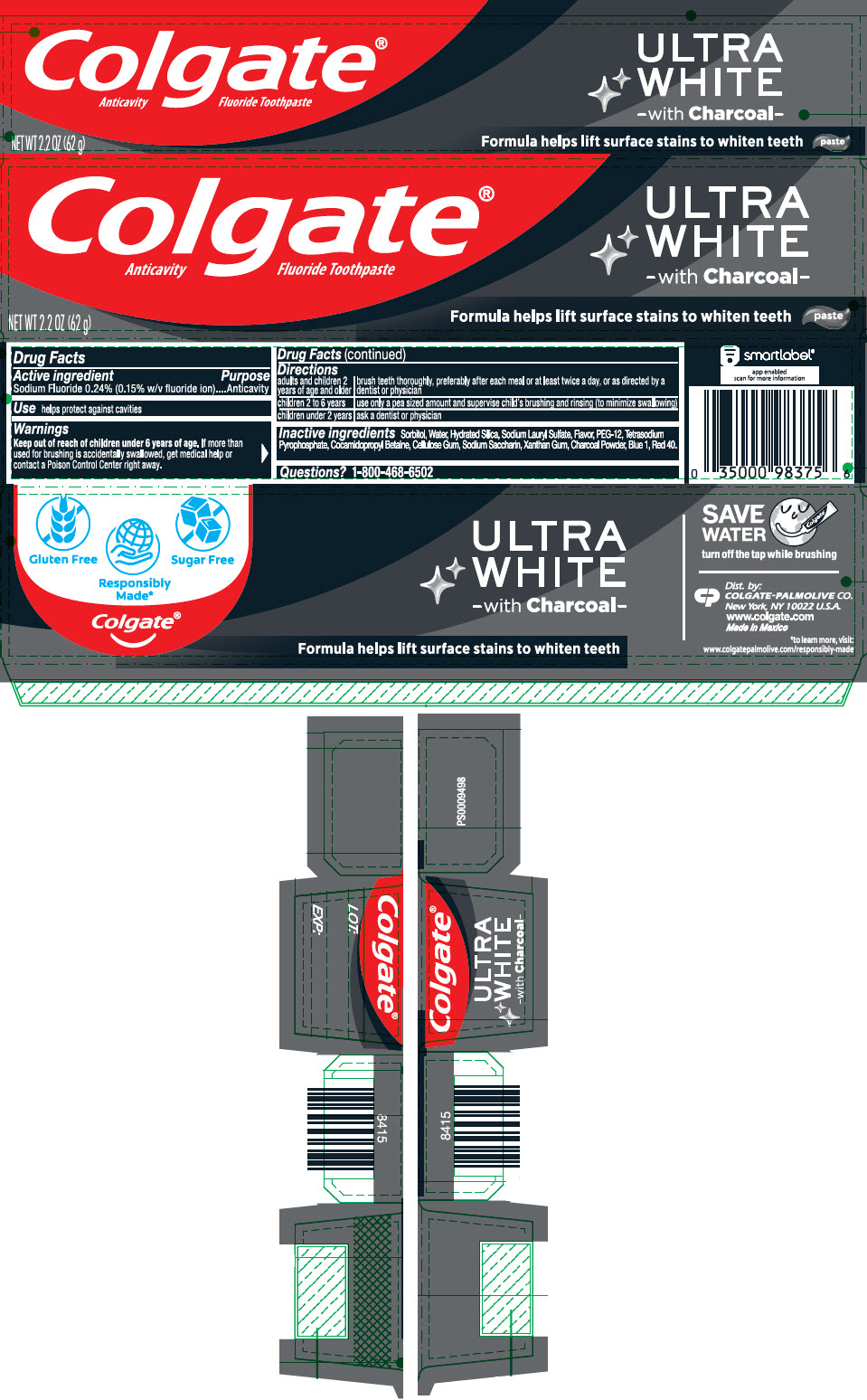 DRUG LABEL: Colgate Ultra White Charcoal
NDC: 35000-418 | Form: PASTE, DENTIFRICE
Manufacturer: Colgate-Palmolive Company
Category: otc | Type: HUMAN OTC DRUG LABEL
Date: 20200731

ACTIVE INGREDIENTS: SODIUM FLUORIDE 1.1 mg/1 g
INACTIVE INGREDIENTS: SORBITOL 630 mg/1 g; WATER; HYDRATED SILICA; SODIUM LAURYL SULFATE; POLYETHYLENE GLYCOL 600; SODIUM PYROPHOSPHATE; COCAMIDOPROPYL BETAINE; CARBOXYMETHYLCELLULOSE SODIUM, UNSPECIFIED; SACCHARIN SODIUM; XANTHAN GUM; ACTIVATED CHARCOAL; FD&C BLUE NO. 1; FD&C RED NO. 40

Colgate® Ultra White Charcoal

Drug Facts

Active ingredient

Sodium Fluoride 0.24% (0.15% w/v fluoride ion)

Purpose

Anticavity

Use

helps protect against cavities

Warnings

Keep out of reach of children under 6 years of age. If more than used for brushing is accidentally swallowed, get medical help or contact a Poison Control Center right away.

Directions

adults and children 2 years of age and older | brush teeth thoroughly, preferably after each meal or at least twice a day, or as directed by a dentist or physician
children 2 to 6 years | use only a pea sized amount and supervise child's brushing and rinsing (to minimize swallowing)
children under 2 years | ask a dentist or physician

Inactive ingredients

Sorbitol, Water, Hydrated Silica, Sodium Lauryl Sulfate, Flavor, PEG-12, Tetrasodium Pyrophosphate, Cocamidopropyl Betaine, Cellulose Gum, Sodium Saccharin, Xanthan Gum, Charcoal Powder, Blue 1, Red 40.

Questions?

1-800-468-6502

Dist. by:
COLGATE-PALMOLIVE CO.
New York, NY 10022 U.S.A.

PRINCIPAL DISPLAY PANEL - 62 g Tube Carton

Colgate®
Anticavity Fluoride Toothpaste

ULTRA
WHITE
- with Charcoal -

Formula helps lift surface stains to whiten teeth
paste

NET WT 2.2 OZ (62 g)